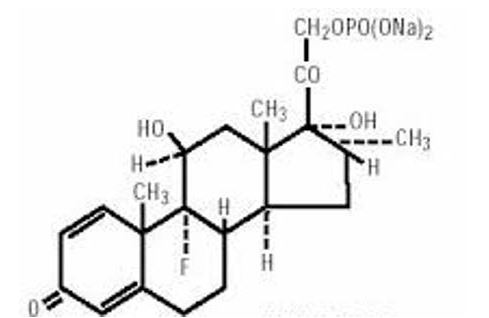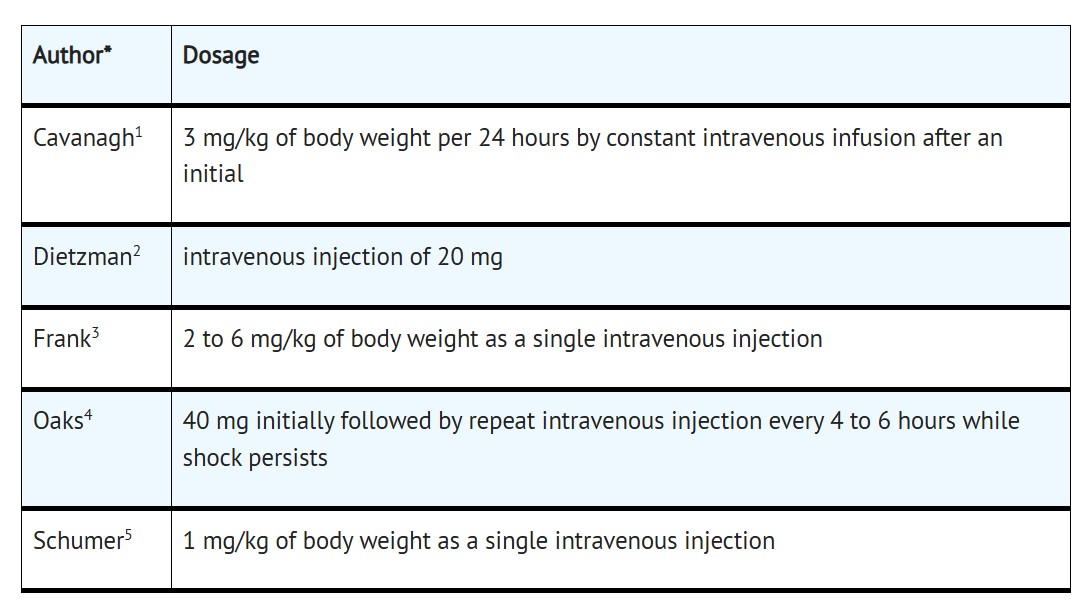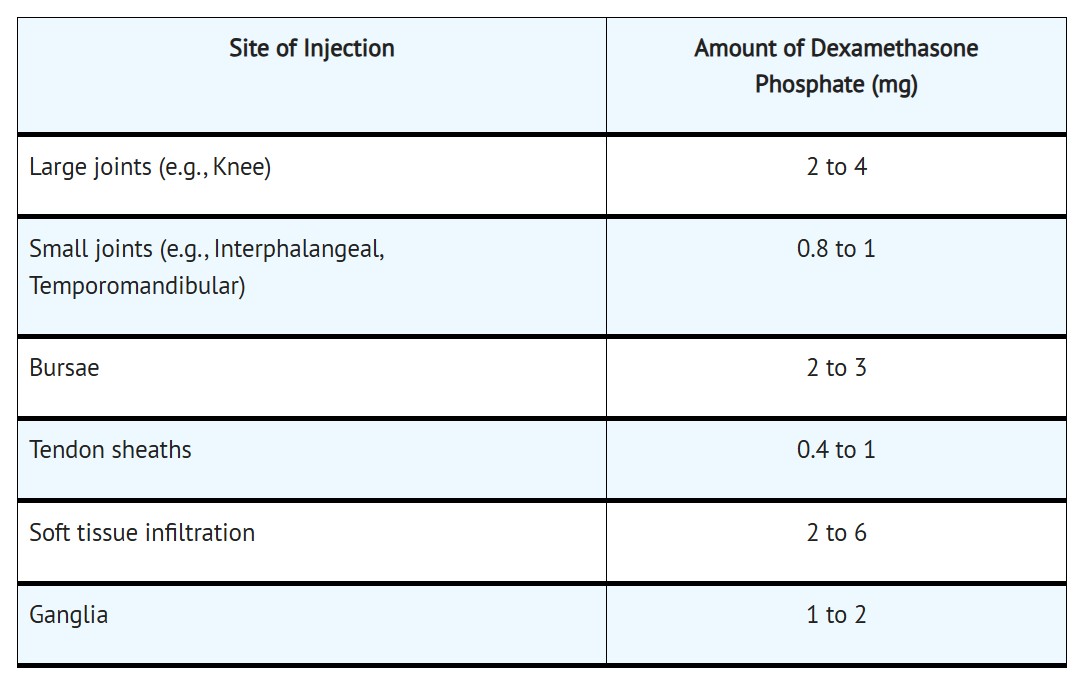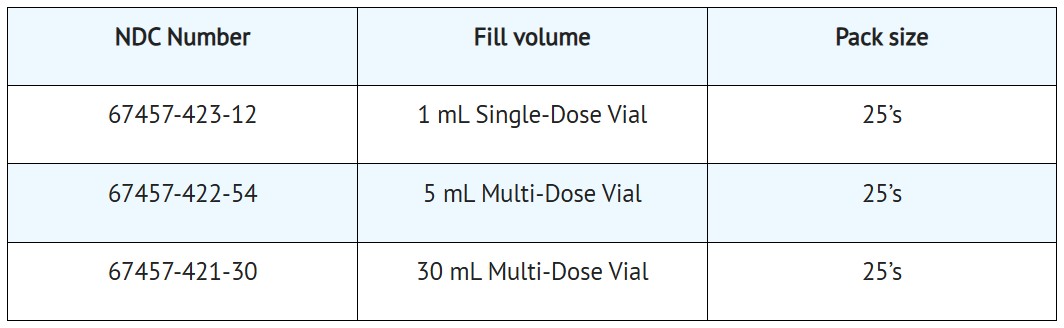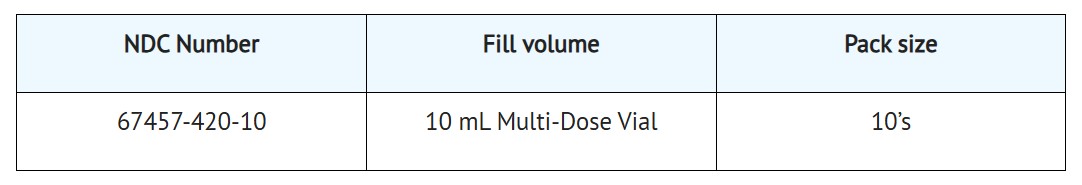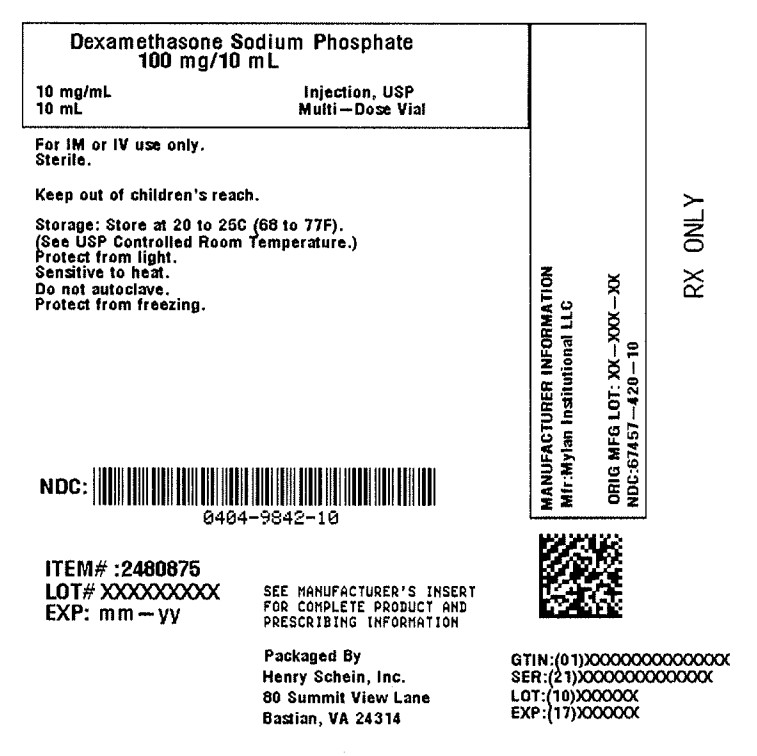 DRUG LABEL: Dexamethasone Sodium Phosphate
NDC: 0404-9842 | Form: INJECTION, SOLUTION
Manufacturer: Henry Schein, Inc.
Category: prescription | Type: HUMAN PRESCRIPTION DRUG LABEL
Date: 20260102

ACTIVE INGREDIENTS: DEXAMETHASONE SODIUM PHOSPHATE 10 mg/1 mL
INACTIVE INGREDIENTS: METHYLPARABEN 1.5 mg/1 mL; propylparaben 0.2 mg/1 mL; EDETATE DISODIUM 0.11 mg/1 mL; ANHYDROUS TRISODIUM CITRATE 10 mg/1 mL; CITRIC ACID MONOHYDRATE; SODIUM HYDROXIDE; WATER

Dexamethasone Sodium Phosphate injection, USP
Rx only

DESCRIPTION

Dexamethasone sodium phosphate, a synthetic adrenocortical steroid, is a white or slightly yellow, crystalline powder. It is freely soluble in water and is exceedingly hygroscopic. The molecular weight is 516.41. It is designated chemically as 9-fluoro-11β,17-dihydroxy-16α-methyl-21-(phosphonooxy)pregna-1,4-diene-3,20-dione disodium salt. The empirical formula is C22H28FNa2O8P and the structural formula is:

Dexamethasone sodium phosphate injection, USP is a sterile solution of dexamethasone sodium phosphate, and is supplied in 4 mg/ mL and 10 mg /mL.

Dexamethasone sodium phosphate injection, USP 4 mg/mL is a sterile solution for intravenous, intramuscular, intra-articular, intralesional and soft tissue administration. Each mL contains:

Active: Dexamethasone sodium phosphate 4.4 mg (equivalent to dexamethasone phosphate 4 mg). Preservatives: Methylparaben 1.5 mg; Propylparaben 0.2 mg. Inactives: Edetate Disodium 0.11 mg; Sodium Citrate Anhydrous 10 mg; Citric Acid and/or Sodium Hydroxide q.s to adjust pH 7.0 to 8.5 and Water for Injection q.s to 1 mL.

Dexamethasone sodium phosphate injection, USP 10 mg/mL is a sterile solution for intravenous or intramuscular use only. Each mL contains:

Actives: Dexamethasone sodium phosphate 11 mg (equivalent to dexamethasone phosphate 10 mg). Preservatives: Methylparaben 1.5 mg; Propylparaben 0.2 mg. Inactives: Edetate Disodium 0.11 mg; Sodium Citrate Anhydrous 10 mg; Citric Acid and/or Sodium Hydroxide q.s to adjust pH 7.0 to 8.5 and Water for Injection q.s to 1 mL.

CLINICAL PHARMACOLOGY

Dexamethasone sodium phosphate injection has a rapid onset but short duration of action when compared with less soluble preparations. Because of this, it is suitable for the treatment of acute disorders responsive to adrenocortical steroid therapy.

Naturally occurring glucocorticoids (hydrocortisone and cortisone), which also have salt-retaining properties, are used as replacement therapy in adrenocortical deficiency states. Their synthetic analogs, including dexamethasone, are primarily used for their potent anti-inflammatory effects in disorders of many organ systems.

Glucocorticoids cause profound and varied metabolic effects. In addition, they modify the body's immune responses to diverse stimuli.

At equipotent anti-inflammatory doses, dexamethasone almost completely lacks the sodium-retaining property of hydrocortisone and closely related derivatives of hydrocortisone.

INDICATIONS AND USAGE

A. By intravenous or intramuscular injection when oral therapy is not feasible

1. Endocrine disorders:

Primary or secondary adrenocortical insufficiency (hydrocortisone or cortisone is the drug of choice; synthetic analogs may be used in conjunction with mineralocorticoids where applicable; in infancy, mineralocorticoid supplementation is of particular importance).

Acute adrenocortical insufficiency (hydrocortisone or cortisone is the drug of choice; mineralocorticoid supplementation may be necessary, particularly when synthetic analogs are used).

Preoperatively, and in the event of serious trauma or illness, in patients with known adrenal insufficiency or when adrenocortical reserve is doubtful.

Shock unresponsive to conventional therapy if adrenocortical insufficiency exists or is suspected.

Congenital adrenal hyperplasia.

Nonsuppurative thyroiditis.

Hypercalcemia associated with cancer.

2. Rheumatic Disorders:

As adjunctive therapy for short-term administration (to tide the patient over an acute episode or exacerbation) in:

Post-traumatic osteoarthritis.

Synovitis of osteoarthritis.

Rheumatoid arthritis, including juvenile rheumatoid arthritis (selected cases may require low-dose maintenance therapy).

Acute and subacute bursitis.

Epicondylitis.

Acute nonspecific tenosynovitis.

Acute gouty arthritis.

Psoriatic arthritis.

Ankylosing spondylitis.

3. Collagen Diseases:

During an exacerbation or as maintenance therapy in selected cases of:

Systemic lupus erythematosus.

Acute rheumatic carditis.

4. Dermatologic Diseases:

Pemphigus.

Severe erythema multiforme. (Stevens-Johnson Syndrome)

Exfoliative dermatitis.

Bullous dermatitis herpetiformis.

Severe seborrheic dermatitis.

Severe psoriasis.

Mycosis fungoides.

5. Allergic States:

Control of severe or incapacitating allergic conditions intractable to adequate trials of conventional treatment in:

Bronchial asthma.

Contact dermatitis.

Atopic dermatitis.

Serum sickness.

Seasonal or perennial allergic rhinitis.

Drug hypersensitivity reactions.

Urticarial transfusion reactions.

Acute noninfectious laryngeal edema (epinephrine is the drug of first choice).

6. Ophthalmic Diseases:

Severe acute and chronic allergic and inflammatory processes involving the eye, such as:

Herpes zoster ophthalmicus.

Iritis, iridocyclitis.

Chorioretinitis.

Diffuse posterior uveitis and choroiditis.

Optic neuritis.

Sympathetic ophthalmia.

Anterior segment inflammation.

Allergic conjunctivitis.

Keratitis.

Allergic corneal marginal ulcers.

7. Gastrointestinal Diseases:

To tide the patient over a critical period of the disease in:

Ulcerative colitis (systemic therapy).

Regional enteritis (systemic therapy).

8. Respiratory Diseases:

Symptomatic sarcoidosis.

Berylliosis.

Fulminating or disseminated pulmonary tuberculosis when used concurrently with appropriate antituberculous chemotherapy.

Loeffler's syndrome not manageable by other means.

Aspiration pneumonitis.

9. Hematologic Disorders:

Acquired (autoimmune) hemolytic anemia.

Idiopathic thrombocytopenic purpura in adults (IV only; IM administration is contraindicated).

Secondary thrombocytopenia in adults.

Erythroblastopenia (RBC anemia).

Congenital (erythroid) hypoplastic anemia.

10. Neoplastic Diseases:

For palliative management of:

Leukemias and lymphomas in adults.

Acute leukemia of childhood.

11. Edematous States:

To induce diuresis or remission of proteinuria in the nephrotic syndrome, without uremia, of the idiopathic type or that due to lupus erythematosus.

12. Miscellaneous:

Tuberculosis meningitis with subarachnoid block or impending block when used concurrently with appropriate antituberculous chemotherapy.

Trichinosis with neurologic or myocardial involvement.

13. Diagnostic testing of adrenocortical hyperfunction.

14. Cerebral Edema associated with primary or metastatic brain tumor, craniotomy, or head injury. Use in cerebral edema is not a substitute for careful neurosurgical evaluation and definitive management such as neurosurgery or other specific therapy.

B. By intra-articular or soft tissue injection

As adjunctive therapy for short-term administration (to tide the patient over an acute episode or exacerbation) in:

Synovitis of osteoarthritis.

Rheumatoid arthritis.

Acute and subacute bursitis.

Acute gouty arthritis.

Epicondylitis.

Acute nonspecific tenosynovitis.

Post-traumatic osteoarthritis.

C. By intralesional injection

Keloids.

Localized hypertrophic, infiltrated, inflammatory lesions of: lichen planus, psoriatic plaques, granuloma annulare, and lichen simplex chronicus (neurodermatitis).

Discoid lupus erythematosus.

Necrobiosis lipoidica diabeticorum.

Alopecia areata.

May also be useful in cystic tumors of an aponeurosis or tendon (ganglia).

CONTRAINDICATIONS

Systemic fungal infections. (See WARNINGS regarding amphotericin B)

WARNINGS

Serious Neurologic Adverse Reactions with Epidural Administration
Serious neurologic events, some resulting in death, have been reported with epidural injection of corticosteroids. Specific events reported include, but are not limited to, spinal cord infarction, paraplegia, quadriplegia, cortical blindness, and stroke. These serious neurologic events have been reported with and without use of fluoroscopy. The safety and effectiveness of epidural administration of corticosteroids has not been established, and corticosteroids are not approved for this use.

In patients on corticosteroid therapy subject to any unusual stress, increased dosage of rapidly acting corticosteroids before, during and after the stressful situation is indicated.

Immunosuppression and Increased Risk of Infection

Corticosteroids, including dexamethasone sodium phosphate injection, (suppress the immune systemand increase the risk of infection with any pathogen, including viral, bacterial,fungal, protozoan, or helminthic pathogens. Corticosteroids can:

• Reduce resistance to new infections
• Exacerbate existing infections
• Increase the risk of disseminated infections
• Increase the risk of reactivation or exacerbation of latent infections
• Mask some signs of infection

Corticosteroid-associated infections can be mild but can be severe and at times fatal. The rate of infectious complications increases with increasing corticosteroid dosages.

Monitor for the development of infection and consider dexamethasone sodium phosphate injection withdrawal or dosage reduction as needed.

Tuberculosis

If dexamethasone sodium phosphate injection is used to treat a condition in patients with latent tuberculosis or tuberculin reactivity, tuberculosis may occur. Closely monitor such patients for reactivation. During prolonged therapy, patients with latent tuberculosis or tuberculin reactivity should receive chemoprophylaxis.

Varicella Zoster and Measles Viral Infections

Varicella and measles can have a serious or even fatal course in non-immune patients taking corticosteroids, including dexamethasone sodium phosphate injection. In corticosteroid-treated patients who have not had these diseases or are nonimmune, particular care should be taken to avoid exposure to varicella and measles:

• If a dexamethasone sodium phosphate injection -treated patient is exposed to varicella, prophylaxis with varicella zoster immune globulin may be indicated. If varicella develops, treatment with antiviral agents may be considered.
• If a dexamethasone sodium phosphate injection - treated patient is exposed to measles, prophylaxis with immunoglobulin may be indicated.

Hepatitis B Virus Reactivation

Hepatitis B virus reactivation can occur in patients who are hepatitis B carriers treated with immunosuppressive dosages of corticosteroids, including dexamethasone sodium phosphate injection. Reactivation can also occur infrequently in corticosteroid-treated patients who appear to have resolved hepatitis B infection. Screen patients for hepatitis B infection before initiating immunosuppressive (e.g., prolonged) treatment with dexamethasone sodium phosphate injection. For patients who show evidence of hepatitis B infection, recommend consultation with physicians with expertise in managing hepatitis B regarding monitoring and consideration for hepatitis B antiviral therapy.

Fungal Infections

Corticosteroids, including dexamethasone sodium phosphate injection, may exacerbate systemic fungal infections; therefore, avoid dexamethasone sodium phosphate injection use in the presence of such infections unless dexamethasone sodium phosphate injection is needed to control drug reactions. For patients on chronic dexamethasone sodium phosphate injection therapy who develop systemic fungal infections, dexamethasone sodium phosphate injection withdrawal or dosage reduction is recommended.

Amebiasis

Corticosteroids, including dexamethasone sodium phosphate injection, may activate latent amebiasis. Therefore, it is recommended that latent amebiasis or active amebiasis be ruled out before initiating dexamethasone sodium phosphate injection in patients who have spent time in the tropics or patients with unexplained diarrhea.

Strongyloides Infestation

Corticosteroids, including dexamethasone sodium phosphate injection, should be used with great care in patients with known or suspected Strongyloides (threadworm) infestation. In such patients, corticosteroid-induced immunosuppression may lead to Strongyloides hyperinfection and dissemination with widespread larval migration, often accompanied by severe enterocolitis and potentially fatal gram-negative septicemia.

Cerebral Malaria

Avoid corticosteroids, including dexamethasone sodium phosphate injection, in patients with cerebral malaria.

Kaposi’s Sarcoma

Kaposi’s sarcoma has been reported to occur in patients receiving corticosteroid therapy, most often for chronic conditions. Discontinuation of corticosteroids may result in clinical improvement of Kaposi’s sarcoma.

Because rare instances of anaphylactoid reactions have occurred in patients receiving parenteral corticosteroid therapy, appropriate precautionary measures should be taken prior to administration, especially when the patient has a history of allergy to any drug. Anaphylactoid and hypersensitivity reactions have been reported for dexamethasone sodium phosphate injection. (See ADVERSE REACTIONS).

Corticosteroids may exacerbate systemic fungal infections and, therefore, should not be used in the presence of such infections unless they are needed to control drug reactions due to amphotericin B. Moreover, there have been cases reported in which concomitant use of amphotericin B and hydrocortisone was followed by cardiac enlargement and congestive failure.

In patients on corticosteroid therapy subjected to any unusual stress, increased dosage of rapidly acting corticosteroids before, during, and after the stressful situation is indicated.

Drug-induced secondary adrenocortical insufficiency may result from too rapid withdrawal of corticosteroids and may be minimized by gradual reduction of dosage. This type of relative insufficiency may persist for months after discontinuation of therapy; therefore, in any situation of stress occurring during that period, hormone therapy should be reinstituted. If the patient is receiving steroids already, dosage may have to be increased. Since mineralocorticoid secretion may be impaired, salt and/or a mineralocorticoid should be administered concurrently.

Moreover, corticosteroids may affect the nitroblue-tetrazolium test for bacterial infection and produce false negative results.

In cerebral malaria, a double-blind trial has shown that the use of corticosteroids is associated with prolongation of coma and a higher incidence of pneumonia and gastrointestinal bleeding.

Prolonged use of corticosteroids may produce posterior subcapsular cataracts, glaucoma with possible damage to the optic nerves, and may enhance the establishment of secondary ocular infections due to fungi or viruses.

Average and large doses of cortisone or hydrocortisone can cause elevation of blood pressure, salt and water retention, and increased excretion of potassium. These effects are less likely to occur with the synthetic derivatives except when used in large doses. Dietary salt restriction and potassium supplementation may be necessary. All corticosteroids increase calcium excretion.

Administration of live virus vaccines, including smallpox, is contraindicated in individuals receiving immunosuppressive doses of corticosteroids. If inactivated viral or bacterial vaccines are administered to individuals receiving immunosuppressive doses of corticosteroids, the expected serum antibody response may not be obtained. However, immunization procedures may be undertaken in patients who are receiving corticosteroids as replacement therapy, e.g., for Addison's disease.

Literature reports suggest an apparent association between use of corticosteroids and left ventricular free wall rupture after a recent myocardial infarction; therefore, therapy with corticosteroids should be used with great caution in these patients.

Usage in Pregnancy
Since adequate human reproduction studies have not been done with corticosteroids, use of these drugs in pregnancy or in women of childbearing potential requires that the anticipated benefits be weighed against the possible hazards to the mother and embryo or fetus. Infants born of mothers who have received substantial doses of corticosteroids during pregnancy should be carefully observed for signs of hypoadrenalism.

Corticosteroids appear in breast milk and could suppress growth, interfere with endogenous corticosteroid production, or cause other unwanted effects. Mothers taking pharmacologic doses of corticosteroids should be advised not to nurse.

PRECAUTIONS

This product, like many other steroid formulations, is sensitive to heat. Therefore, it should not be autoclaved when it is desirable to sterilize the exterior of the vial.

Following prolonged therapy, withdrawal of corticosteroids may result in symptoms of the corticosteroid withdrawal syndrome including fever, myalgia, arthralgia, and malaise. This may occur in patients even without evidence of adrenal insufficiency.

There is an enhanced effect of corticosteroids in patients with hypothyroidism and in those with cirrhosis.

Corticosteroids should be used cautiously in patients with ocular herpes simplex for fear of corneal perforation.

The lowest possible dose of corticosteroid should be used to control the condition under treatment, and when reduction in dosage is possible, the reduction must be gradual.

Psychic derangements may appear when corticosteroids are used, ranging from euphoria, insomnia, mood swings, personality changes, and severe depression to frank psychotic manifestations. Also, existing emotional instability or psychotic tendencies may be aggravated by corticosteroids.

Aspirin should be used with caution in conjunction with corticosteroids in hypoprothrombinemia.

Steroids should be used with caution in nonspecific ulcerative colitis, if there is a probability of impending perforation, abscess, or other pyogenic infection, also in diverticulitis, fresh intestinal anastomoses, active or latent peptic ulcer, renal insufficiency, hypertension, osteoporosis, and myasthenia gravis. Signs of peritoneal irritation following gastrointestinal perforation in patients receiving large doses of corticosteroids may be minimal or absent. Fat embolism has been reported as a possible complication of hypercortisonism.

When large doses are given, some authorities advise that antacids be administered between meals to help prevent peptic ulcer.

Growth and development of infants and children on prolonged corticosteroid therapy should be carefully followed.

Steroids may increase or decrease motility and number of spermatozoa in some patients.

Phenytoin, phenobarbital, ephedrine, and rifampin may enhance the metabolic clearance of corticosteroids, resulting in decreased blood levels and lessened physiologic activity, thus requiring adjustment in corticosteroid dosage. These interactions may interfere with dexamethasone suppression tests which should be interpreted with caution during administration of these drugs.

False negative results in the dexamethasone suppression test (DST) in patients being treated with indomethacin have been reported. Thus, results of the DST should be interpreted with caution in these patients.

The prothrombin time should be checked frequently in patients who are receiving corticosteroids and coumarin anticoagulants at the same time because of reports that corticosteroids have altered the response to these anticoagulants. Studies have shown that the usual effect produced by adding corticosteroids is inhibition of response to coumarins, although there have been some conflicting reports of potentiation not substantiated by studies.

When corticosteroids are administered concomitantly with potassium depleting diuretics, patients should be observed closely for development of hypokalemia.

Intra-articular injection of a corticosteroid may produce systemic as well as local effects.

Appropriate examination of any joint fluid present is necessary to exclude a septic process.

A marked increase in pain accompanied by local swelling, further restriction of joint motion, fever, and malaise is suggestive of septic arthritis. If this complication occurs and the diagnosis of sepsis is confirmed, appropriate antimicrobial therapy should be instituted.

Injection of a steroid into an infected site is to be avoided.

Corticosteroids should not be injected into unstable joints.

Patients should be impressed strongly with the importance of not overusing joints in which symptomatic benefit has been obtained as long as the inflammatory process remains active.

Frequent intra-articular injection may result in damage to joint tissues.

The slower rate of absorption by intramuscular administration should be recognized.

Information for Patients

Susceptible patients who are on immunosuppressant doses of corticosteroids should be warned to avoid exposure to chickenpox or measles. Patients should also be advised that if they are exposed, medical advice should be sought without delay.

ADVERSE REACTIONS

Fluid and electrolyte disturbances
Sodium retention

Fluid retention

Congestive heart failure in susceptible patients

Potassium loss

Hypokalemic alkalosis

Hypertension

Musculoskeletal
Muscle weakness

Steroid myopathy

Loss of muscle mass

Osteoporosis

Vertebral compression fractures

Aseptic necrosis of femoral and humeral heads

Tendon rupture

Pathologic fracture of long bones

Gastrointestinal
Peptic ulcer with possible subsequent perforation and hemorrhage

Perforation of the small and large bowel; particularly in patients with inflammatory bowel disease

Pancreatitis

Abdominal distention

Ulcerative esophagitis

Dermatologic
Impaired wound healing

Thin fragile skin

Petechiae and ecchymoses

Erythema

Increased sweating

May suppress reactions to skin tests

Burning or tingling especially in the perineal area (after IV injection) other cutaneous reactions, such as allergic dermatitis, urticaria, angioneurotic edema

Neurologic
Convulsions

Increased intracranial pressure with papilledema (pseudotumor cerebri) usually after treatment

Vertigo

Headache

Psychic disturbances

Endocrine
Menstrual irregularities

Development of cushingoid state

Suppression of growth in children

Secondary adrenocortical and pituitary unresponsiveness, particularly in times of stress, as in trauma, surgery, or illness

Decreased carbohydrate tolerance

Manifestations of latent diabetes mellitus

Increased requirements for insulin or oral hypoglycemic agents in diabetics

Hirsutism

Ophthalmic
Posterior subcapsular cataracts

Increased intraocular pressure

Glaucoma

Exophthalmos

Metabolic
Negative nitrogen balance due to protein catabolism

Cardiovascular
Myocardial rupture following recent myocardial infarction. (See WARNINGS).

Other
Anaphylactoid or hypersensitivity reactions

Thromboembolism

Weight gain

Increased appetite

Nausea

Malaise

Hiccups

The following additional adverse reactions are related to parenteral corticosteroid therapy:

Rare instances of blindness associated with intralesional therapy around the face and head

Hyperpigmentation or hypopigmentation

Subcutaneous and cutaneous atrophy

Sterile abscess

Post-injection flare (following intra-articular use)

Charcot-like arthropathy

OVERDOSAGE

Reports of acute toxicity and/or death following overdosage of glucocorticoids are rare. In the event of overdosage, no specific antidote is available; treatment is supportive and symptomatic.

The oral LD50 of dexamethasone in female mice was 6.5 g/kg. The intravenous LD50 of dexamethasone sodium phosphate in female mice was 794 mg/kg.

DOSAGE AND ADMINISTRATION

Dexamethasone sodium phosphate injection, USP 4 mg/mL is for intravenous, intramuscular, intra-articular, intralesional and soft tissue injection.

Dexamethasone sodium phosphate injection, USP 10 mg/mL is for intravenous or intramuscular use only.

Dexamethasone sodium phosphate injection, USP can be given directly from the vial, or it can be added to sodium chloride injection or dextrose injection and administered by intravenous drip.

Solutions used for intravenous administration or further dilution of this product should be preservative-free when used in the neonate, especially the premature infant.

When it is mixed with an infusion solution, sterile precautions should be observed. Since infusion solutions generally do not contain preservatives, mixtures should be used within 24 hours.

DOSAGE REQUIREMENTS ARE VARIABLE AND MUST BE INDIVIDUALIZED ON THE BASIS OF THE DISEASE AND THE RESPONSE OF THE PATIENT.

A. Intravenous and Intramuscular Injection
The initial dosage of dexamethasone sodium phosphate injection varies from 0.5 to 9 mg a day depending on the disease being treated. In less severe diseases doses lower than 0.5 mg may suffice, while in severe diseases doses higher than 9 mg may be required.

The initial dosage should be maintained or adjusted until the patient's response is satisfactory. If a satisfactory clinical response does not occur after a reasonable period of time, discontinue dexamethasone sodium phosphate injection and transfer the patient to other therapy.

After a favorable initial response, the proper maintenance dosage should be determined by decreasing the initial dosage in small amounts to the lowest dosage that maintains an adequate clinical response.

Patients should be observed closely for signs that might require dosage adjustment, including changes in clinical status resulting from remissions or exacerbations of the disease, individual drug responsiveness, and the effect of stress (e.g., surgery, infection, trauma). During stress it may be necessary to increase dosage temporarily.

If the drug is to be stopped after more than a few days of treatment, it usually should be withdrawn gradually.

When the intravenous route of administration is used, dosage usually should be the same as the oral dosage. In certain overwhelming, acute, life-threatening situations, however, administration in dosages exceeding the usual dosages may be justified and may be in multiples of the oral dosages. The slower rate of absorption by intramuscular administration should be recognized.

Shock

There is a tendency in current medical practice to use high (pharmacologic) doses of corticosteroids for the treatment of unresponsive shock. The following dosages of dexamethasone sodium phosphate injection have been suggested by various authors:

Administration of high dose corticosteroid therapy should be continued only until the patient's condition has stabilized and usually not longer than 48 to 72 hours.

Although adverse reactions associated with high dose, short term corticosteroid therapy are uncommon, peptic ulceration may occur.

Cerebral Edema
Dexamethasone sodium phosphate injection is generally administered initially in a dosage of 10 mg intravenously followed by four mg every six hours intramuscularly until the symptoms of cerebral edema subside. Response is usually noted within 12 to 24 hours and dosage may be reduced after two to four days and gradually discontinued over a period of five to seven days. For palliative management of patients with recurrent or inoperable brain tumors, maintenance therapy with two mg two or three times a day may be effective.

Acute Allergic Disorders
In acute, self-limited allergic disorders or acute exacerbations of chronic allergic disorders, the following dosage schedule combining parenteral and oral therapy is suggested:

Dexamethasone sodium phosphate injection, USP 4 mg/mL; first day, 1 or 2 mL (4 or 8 mg), intramuscularly.

Dexamethasone sodium phosphate tablets, 0.75 mg; second and third days, 4 tablets in two divided doses each day; fourth day, 2 tablets in two divided doses; fifth and sixth days, 1 tablet each day; seventh day, no treatment; eighth day, follow-up visit.

This schedule is designed to ensure adequate therapy during acute episodes, while minimizing the risk of overdosage in chronic cases.

B. Intra-Articular, Intralesional and Soft Tissue Injection
Intra-articular, intralesional and soft tissue injections are generally employed when affected joints or areas are limited to one or two sites. Dosage and frequency of injection varies depending on the condition and the site of injection. The usual dose is from 0.2 to 6 mg. The frequency usually ranges from once every three to five days to once every two to three weeks. Frequent intra-articular injection may result in damage to joint tissues.

Some of the usual single doses are:

Parenteral drug products should be inspected visually for particulate matter and discoloration prior to administration, whenever the solution and container permit.

Dexamethasone sodium phosphate injection, USP is particularly recommended for use in conjunction with one of the less soluble, longer-acting steroids for intra-articular and soft tissue injection.

HOW SUPPLIED

Dexamethasone sodium phosphate injection, USP 4 mg/mL is for-intravenous, intramuscular, intra-articular, intralesional and soft tissue administration available as follows:

Dexamethasone sodium phosphate injection, USP 10 mg/mL is for intravenous and intramuscular injection only available as follows:

Store at 20° to 25°C (68° to 77°F). [See USP Controlled Room Temperature.]

Protect from light.

Sensitive to heat. Do not autoclave. Protect from freezing.

Product repackaged by: Henry Schein, Inc., Bastian, VA 24314
From Original Manufacturer/Distributor's NDC and Unit of Sale | To Henry Schein Repackaged Product NDC and Unit of Sale | Total Strength/Total Volume (Concentration) per unit
NDC 67457-420-10 Pack of 10 Multi-Dose Vials | NDC 0404-9842-10 1 10 mL Multi-Dose vial in a bag (Vial bears NDC 67457-420-00) | 10 mg/mL
NDC 67457-421-30 Pack of 25 Multi-Dose Vials | NDC 0404-9795-30 1 30 mL Multi-Dose vial in a bag (Vial bears NDC 67457-421-00) | 4 mg/mL

REFERENCES

- Cavanagh, D.; Singh, K. B.: Endotoxin shock in pregnancy and abortion, in: "Corticosteroids in the Treatment of Shock," Schumer, W.; Nyhus, L. M., Editors, Urbana, University of Illinois Press, 1970, pp. 86–96.
- • Dietzman, R. H.; Ersek, R. A.; Bloch, J. M.; Lilleher, R. C.: High-output, low-resistance gram-negative septic shock in man, Angiology 20: 691–700, Dec. 1969.
- • Frank, E.: Clinical observations in shock and management (in: Shields, T. F., ed.: Symposium on current concepts and management of shocks), J. Maine Med. Ass. 59: 195 – 200, Oct. 1968.
- • Oaks, W. W.; Cohen, H. E.: Endotoxin shock in the geriatric patient, Geriat. 22: 120–130, Mar. 1967.
- • Schumer, W.; Nyhus, L. M.: Corticosteroid effect on biochemical parameters of human oligemic shock, Arch. Surg. 100: 405–408, Apr. 1970.

Manufactured for:
Mylan Institutional LLC
Morgantown, WV 26505 U.S.A.

Manufactured by:
Mylan Laboratories Limited
Bangalore, India

MARCH 2024